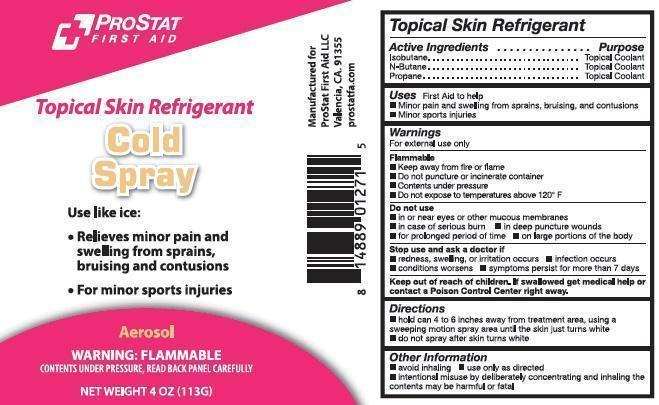 DRUG LABEL: ProStat Cold Spray
NDC: 58228-0101
Manufacturer: ProStat First Aid
Category: other | Type: OTC MEDICAL DEVICE LABEL
Date: 20140224

ProStat Topical Skin Refrigerant Cold Spray

Active Ingredients

Isobutane
N-Butane
Propane

Purpose

Topical Coolant
Topical Coolant
Topical Coolant

Uses

First aid to help

minor pain and swelling from sprains, bruising, and contusion
minor sports injuries

Warnings

For external use only

Flammable
keep away from fire or flame
contents under pressure
do not puncture or incinerate container
do not expose to temperatures above 120° F

Do not use

in or near eyes or other mucous membranes
in case of serious burns
in deep puncture wounds
for a prolonged period of time
on a large portion of the body

Stop use and ask a doctor if

redness, swelling or irritation occurs
infection occurs
condition worsens
symptoms persist for more than 7 days

Directions

hold can 4-6 inches away from treatment area, using a sweeping motion
spray area until skin just turns white
do not spray after skin turns white

Other information

avoid inhaling
use only as directed
intentional misuse by deliberately concentrating and inhaling the contents may be harmful or fatal